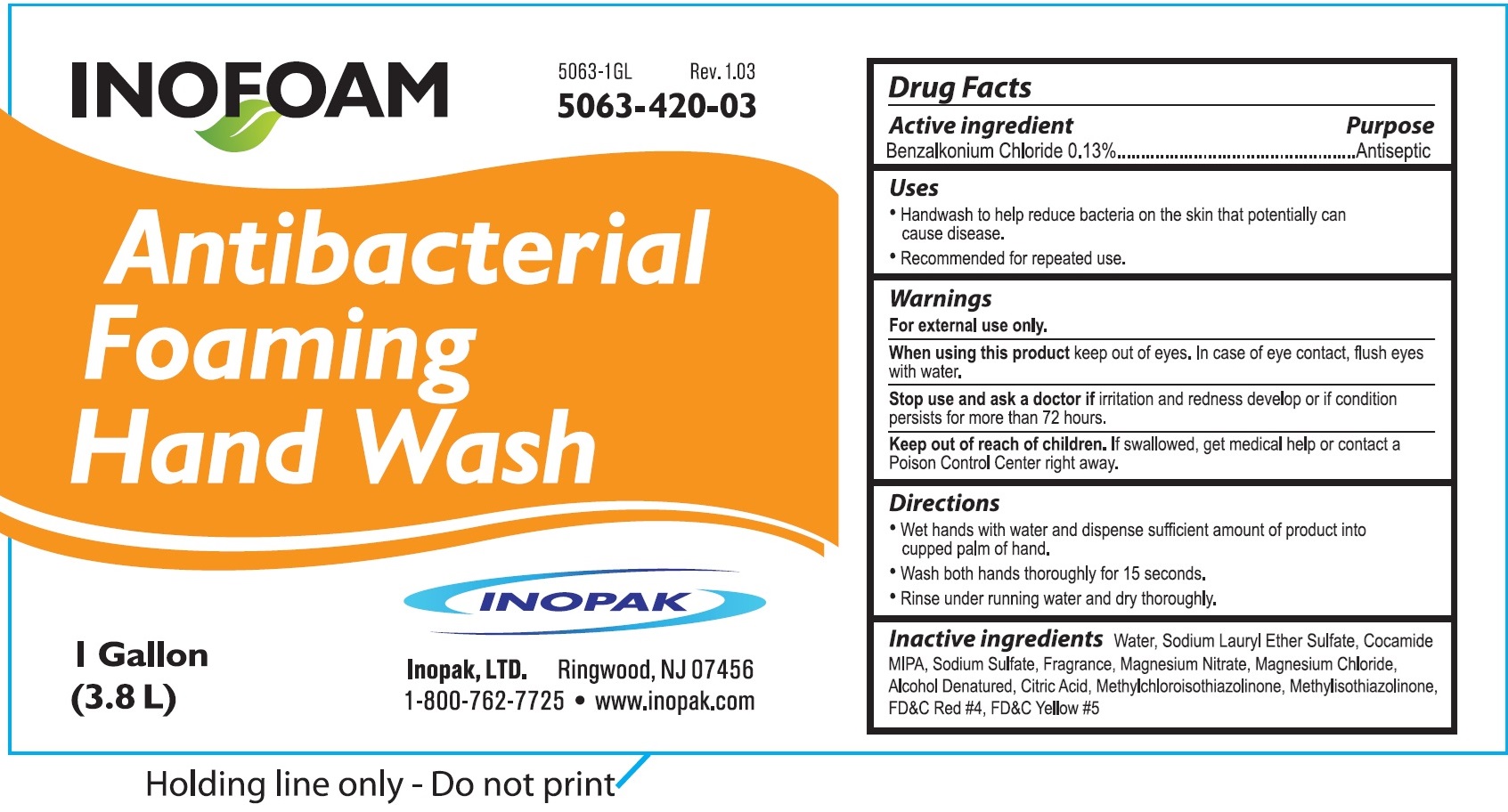 DRUG LABEL: Inofoam Antibacterial Foaming Hand Wash
NDC: 73062-032 | Form: LIQUID
Manufacturer: Avro Enterprises, LLC
Category: otc | Type: HUMAN OTC DRUG LABEL
Date: 20231117

ACTIVE INGREDIENTS: BENZALKONIUM CHLORIDE 1.3 mg/1 mL
INACTIVE INGREDIENTS: WATER; SODIUM LAURETH-3 SULFATE; COCO MONOISOPROPANOLAMIDE; SODIUM SULFATE; MAGNESIUM NITRATE; MAGNESIUM CHLORIDE; ALCOHOL; CITRIC ACID MONOHYDRATE; METHYLCHLOROISOTHIAZOLINONE; METHYLISOTHIAZOLINONE; FD&C RED NO. 4; FD&C YELLOW NO. 5

Inofoam Antibacterial Foaming Hand Wash

Active ingredient

Benzalkonium Chloride 0.13%

Purppose

Antiseptic

Uses

- Handwash to help reduce bacteria on the skin that potentially can cause disease.
- Recommended for repeated use.

Warings

For external use only.

When using this product

Keep out of eyes. In case of eye contact, flush eyes with water.

Stop use and ask a doctor if

irritation and redness develop or if condition persists for more than 72 hours.

Keep out of reach of children.

If swallowed, get medical help or contact a Poison Control Center right away.

Directions

• Wet hands with water and dispense sufficient amount of product into cupped palm of hand. • Wash both hands thoroughly for 15 seconds. • Rinse under running water and dry thoroughly.

Inactive ingredients

Water, Sodium Lauryl Ether Sulfate, Cocamide MIPA, Sodium Sulfate, Fragrance, Magnesium Nitrate, Magnesium Chloride, Alcohol Denatured, Citric Acid, Methylchloroisothiazolinone, Methylisothiazolinone, FD&C Red#4, FD&C Yellow #5